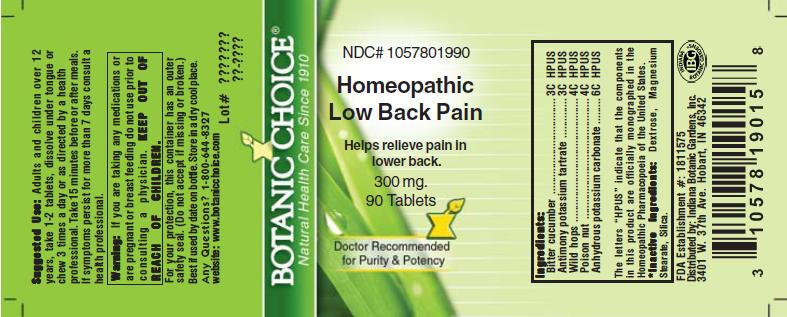 DRUG LABEL: Homeopathic Low Back Pain Formula
NDC: 10578-019 | Form: TABLET
Manufacturer: Indiana Botanic Gardens
Category: homeopathic | Type: HUMAN OTC DRUG LABEL
Date: 20110325

ACTIVE INGREDIENTS: CITRULLUS COLOCYNTHIS FRUIT PULP 3 [hp_C]/1 1; ANTIMONY POTASSIUM TARTRATE 3 [hp_C]/1 1; POTASSIUM CARBONATE 6 [hp_C]/1 1; BRYONIA ALBA ROOT 4 [hp_C]/1 1; STRYCHNOS NUX-VOMICA SEED 4 [hp_C]/1 1
INACTIVE INGREDIENTS: DEXTROSE; MAGNESIUM STEARATE ; SILICON DIOXIDE 

Homeopathic Low Back Pain Formula

ACTIVE INGREDIENT

I n g r e d i e n t s :

Bitter cucumber................................ 3C HPUS
Antimony potassium tartrate........................ 3C HPUS
Wild hops............................ 4C HPUS
Poison nut..................................... 4C HPUS
Anhydrous potassium carbonate............................... 6C HPUS

The letters “HPUS” indicate that the components in
this product are officially monographed in the
Homeopathic Pharmacopoeia of the United States.

PURPOSE

Helps relieve pain in lower back

KEEP OUT OF
REACH OF CHILDREN.

INDICATIONS AND USAGE

Helps relieve pain in lower back

WARNINGS

Warning: If you are taking any medications or
are pregnant or breast feeding do not use prior to
consulting a physician.

DOSAGE AND ADMINISTRATION

Suggested Use: Adults and children over 12
years, take 1-2 tablets, dissolve under tongue or
chew 3 times a day or as directed by a health care
professional. Take 15 minutes before or after meals.
If symptoms persist for more than 7 days consult a
health professional.

Inactive Ingredients: Dextrose, Magnesium
Stearate, Silica.

PACKAGE LABEL

NDC# 1057801990

Homeopathic Low Back Pain Formula

Helps relieve pain in lower back

300 mg.
90 Tablets

USER SAFETY WARNINGS

For your protection, this container has an outer
safety seal. (Do not accept if missing or broken.)
Best if used by date on bottle. Store in a dry cool place.
Any Questions? 1-800-644-8327
website: www.botanicchoice.com

FDA Establishment #: 1811575

Distributed by: Indiana Botanic Gardens, Inc.
3401 W. 37th Ave. Hobart, IN 46342